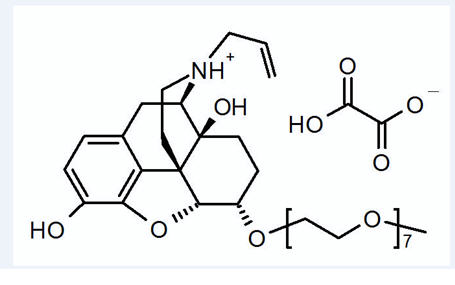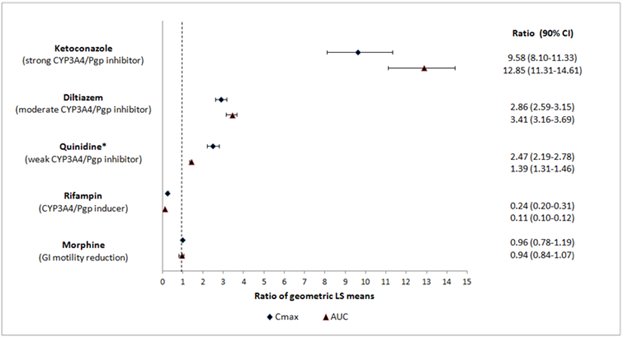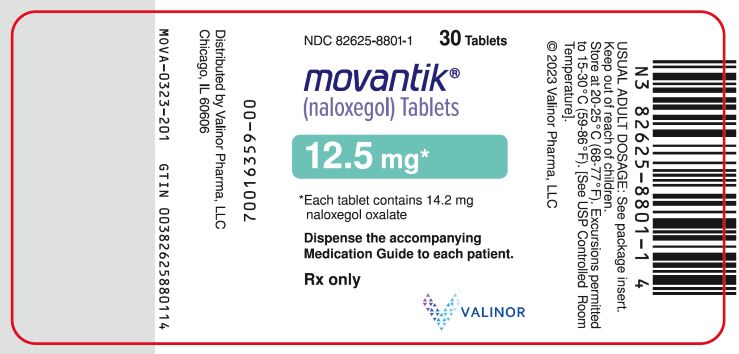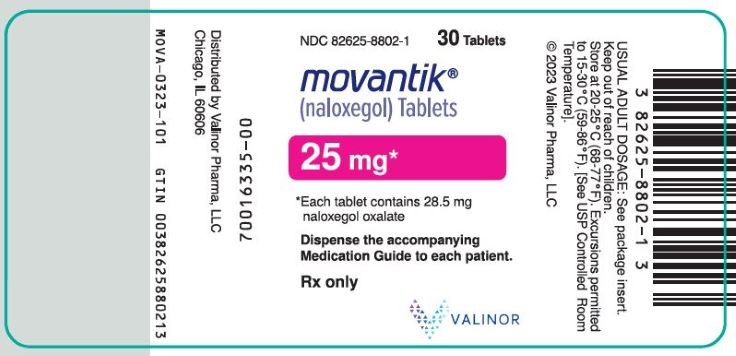 DRUG LABEL: MOVANTIK
NDC: 82625-8801 | Form: TABLET, FILM COATED
Manufacturer: Valinor Pharma, LLC
Category: prescription | Type: HUMAN PRESCRIPTION DRUG LABEL
Date: 20251222

ACTIVE INGREDIENTS: NALOXEGOL OXALATE 12.5 mg/1 1
INACTIVE INGREDIENTS: MANNITOL; MICROCRYSTALLINE CELLULOSE; CROSCARMELLOSE SODIUM; MAGNESIUM STEARATE; PROPYL GALLATE; HYPROMELLOSE, UNSPECIFIED; TITANIUM DIOXIDE; POLYETHYLENE GLYCOL 400; FERRIC OXIDE RED; FERROSOFERRIC OXIDE; WATER

HIGHLIGHTS OF PRESCRIBING INFORMATION

These highlights do not include all the information needed to use MOVANTIK safely and effectively. See full prescribing information for MOVANTIK.
MOVANTIK®(naloxegol) tablets, for oral use
Initial U.S. Approval: 2014

RECENT MAJOR CHANGES

Warnings and Precautions (5.3) 04/2020

1 INDICATIONS AND USAGE

MOVANTIK is an opioid antagonist indicated for the treatment of opioid-induced constipation (OIC) in adult patients with chronic non-cancer pain, including patients with chronic pain related to prior cancer or its treatment who do not require frequent (e.g., weekly) opioid dosage escalation. (1)

2 DOSAGE AND ADMINISTRATION

Administration:

- Discontinue maintenance laxative therapy before starting MOVANTIK; may resume laxatives if patients have OIC symptoms after taking MOVANTIK for 3 days. (2.1)
- Alteration in analgesic dosing regimen prior to starting MOVANTIK is not required. (2.1)
- Patients receiving opioids for less than 4 weeks may be less responsive to MOVANTIK. (2.1)
- Take on an empty stomach at least 1 hour prior to the first meal of the day or 2 hours after the meal. (2.1)
- For patients who are unable to swallow the MOVANTIK tablet whole, the tablet can be crushed and given orally or administered via nasogastric tube, see full prescribing information. (2.1)
- Avoid consumption of grapefruit or grapefruit juice. (2.1, 7.1)
- Discontinue if treatment with the opioid pain medication is also discontinued. (2.1)

Recommended dosage:

- 25 mg once daily; if not tolerated, reduce to 12.5 mg once daily. (2.2)
- Renal Impairment (CLcr < 60 mL/min): 12.5 mg once daily; increase to 25 mg once daily if tolerated and monitor for adverse reactions. (2.3, 8.6)

3 DOSAGE FORMS AND STRENGTHS

- Tablets: 12.5 mg and 25 mg (3)

4 CONTRAINDICATIONS

- Patients with known or suspected gastrointestinal obstruction and at risk of recurrent obstruction. (4, 5.3)
- Concomitant use with strong CYP3A4 inhibitors (e.g., clarithromycin, ketoconazole). (4, 7.1)
- Known serious or severe hypersensitivity reaction to MOVANTIK or any of its excipients. (4)

5 WARNINGS AND PRECAUTIONS

- Opioid withdrawal: Consider the overall risk benefit in patients with disruptions to the blood-brain barrier. Monitor for symptoms of opioid withdrawal. (5.1)
- Severe abdominal pain and/or diarrhea: Monitor for the development of symptoms after initiating treatment with MOVANTIK and discontinue if severe symptoms develop. Consider restarting MOVANTIK at 12.5 mg once daily if appropriate. (5.2)
- Gastrointestinal perforation: Consider the overall risk benefit in patients with known or suspected lesions of the GI tract. Monitor for severe, persistent or worsening abdominal pain; discontinue if development of symptoms. (5.3)

6 ADVERSE REACTIONS

The most common adverse reactions in clinical trials (≥3%) are: abdominal pain, diarrhea, nausea, flatulence, vomiting, and headache. (6.1)

To report SUSPECTED ADVERSE REACTIONS, contact Valinor at 1-877-592-2337 or FDA at 1-800-FDA-1088 or www.fda.gov/medwatch.

7 DRUG INTERACTIONS

- Moderate CYP3A4 inhibitors (e.g., diltiazem, erythromycin, verapamil): Increased naloxegol concentrations; avoid concomitant use; if unavoidable, reduce dosage to 12.5 mg once daily and monitor for adverse reactions. (2.4, 7.1)
- Strong CYP3A4 inducers (e.g., rifampin): Decreased concentrations of naloxegol; concomitant use is not recommended. (7.1)
- Other opioid antagonists: Potential for additive effect and increased risk of opioid withdrawal; avoid concomitant use. (7.1)

8 USE IN SPECIFIC POPULATIONS

- Pregnancy: May precipitate opioid withdrawal in pregnant women and the fetus. (8.1)
- Lactation: Breastfeeding not recommended. (8.2)
- Hepatic Impairment: Avoid in severe impairment. (8.7)

FULL PRESCRIBING INFORMATION

1 INDICATIONS AND USAGE

MOVANTIK®is indicated for the treatment of opioid-induced constipation (OIC) in adult patients with chronic non-cancer pain, including patients with chronic pain related to prior cancer or its treatment who do not require frequent (e.g., weekly) opioid dosage escalation.

2 DOSAGE AND ADMINISTRATION

2.1 Administration Instructions

- Discontinue all maintenance laxative therapy prior to initiation of MOVANTIK. Laxative(s) can be used as needed if there is a suboptimal response to MOVANTIK after three days.
- Alteration in analgesic dosing regimen prior to initiating MOVANTIK is not required.
- Patients receiving opioids for less than 4 weeks may be less responsive to MOVANTIK [see Clinical Studies (14)] .
- Take MOVANTIK on an empty stomach at least 1 hour prior to the first meal of the day or 2 hours after the meal.
- For patients who are unable to swallow the MOVANTIK tablet whole, the tablet can be crushed to a powder, mixed with 4 ounces (120 mL) of water, and drunk immediately. The glass should be refilled with 4 ounces (120 mL) of water, stirred and the contents drunk.
- MOVANTIK can also be administered via a nasogastric (NG) tube, as follows:

1.Flush the NG tube with 1 ounce (30 mL) of water using a 60 mL syringe.

2.Crush the tablet to a powder in a container and mix with approximately 2 ounces (60 mL) of water.

3.Draw up the mixture using the 60 mL syringe and administer the syringe contents through the NG tube.

4.Add approximately 2 ounces (60 mL) of water to the same container used to prepare the dose of MOVANTIK.

5.Draw up the water using the same 60 mL syringe and use all the water to flush the NG tube and any remaining medicine from the NG tube into the stomach.

- Avoid consumption of grapefruit or grapefruit juice during treatment with MOVANTIK.
- Discontinue MOVANTIK if treatment with the opioid pain medication is also discontinued.

2.2 Adult Dosage

The recommended MOVANTIK dosage is 25 mg once daily in the morning. If patients are not able to tolerate MOVANTIK, reduce the dosage to 12.5 mg once daily [see Clinical Pharmacology (12.2)] .

2.3 Dosage in Adult Patients with Renal Impairment

The starting dosage for patients with creatinine clearance (CLcr) <60 mL/min (i.e., patients with moderate, severe, or end-stage renal impairment) is 12.5 mg once daily. If this dosage is well tolerated but OIC symptoms continue, the dosage may be increased to 25 mg once daily taking into consideration the potential for markedly increased exposures in some patients with renal impairment and the increased risk of adverse reactions with higher exposures [see Use in Specific Populations (8.6)and Clinical Pharmacology (12.3)] .

2.4 Dosage Recommendations due to Drug Interactions

Avoid concomitant use of MOVANTIK with moderate CYP3A4 inhibitor drugs (e.g., diltiazem, erythromycin, verapamil). If concurrent use is unavoidable, reduce the MOVANTIK dosage to 12.5 mg once daily and monitor for adverse reactions [see Drug Interactions (7.1)and Clinical Pharmacology (12.3)] .

3 DOSAGE FORMS AND STRENGTHS

MOVANTIK (naloxegol) is available in two strengths:

• Tablets: 12.5 mg supplied as mauve, oval, biconvex, film-coated, intagliated with “nGL” on one side and “12.5” on the other side.
• Tablets: 25 mg supplied as mauve, oval, biconvex, film-coated, intagliated with “nGL” on one side and “25” on the other side.

4 CONTRAINDICATIONS

MOVANTIK is contraindicated in:

- Patients with known or suspected gastrointestinal obstruction and patients at risk of recurrent obstruction, due to the potential for gastrointestinal perforation [see Warnings and Precautions (5.3)].
- Patients concomitantly using strong CYP3A4 inhibitors (e.g., clarithromycin, ketoconazole) because these medications can significantly increase exposure to naloxegol which may precipitate opioid withdrawal symptoms such as hyperhidrosis, chills, diarrhea, abdominal pain, anxiety, irritability, and yawning [see Drug Interactions (7.1)and Clinical Pharmacology (12.3)].
- Patients who have had a known serious or severe hypersensitivity reaction to MOVANTIK or any of its excipients [see Adverse Reactions (6.2)] .

5 WARNINGS AND PRECAUTIONS

5.1 Opioid Withdrawal

Clusters of symptoms consistent with opioid withdrawal, including hyperhidrosis, chills, diarrhea, abdominal pain, anxiety, irritability, and yawning have occurred in patients treated with MOVANTIK [see Adverse Reactions (6.1)] . In addition, patients receiving methadone as therapy for their pain condition were observed in clinical trials to have a higher frequency of gastrointestinal adverse reactions that may have been related to opioid withdrawal than patients receiving other opioids [see Adverse Reactions (6.1)] . Patients having disruptions to the blood-brain barrier may be at increased risk for opioid withdrawal or reduced analgesia. Take into account the overall risk-benefit profile when using MOVANTIK in such patients. Monitor for symptoms of opioid withdrawal in such patients.

5.2 Severe Abdominal Pain and/or Diarrhea

Reports of severe abdominal pain and/or diarrhea have been reported, some of which resulted in hospitalization. Most of the cases of severe abdominal pain were reported in patients taking the 25 mg dosage. Symptoms generally occurred within a few days of initiation of MOVANTIK. Monitor patients for the development of abdominal pain and/or diarrhea with MOVANTIK and discontinue therapy if severe symptoms occur. Consider restarting MOVANTIK at 12.5 mg once daily, if appropriate.

5.3 Gastrointestinal Perforation

Cases of gastrointestinal (GI) perforation have been reported with use of peripherally acting opioid antagonists, including MOVANTIK. Postmarketing cases of GI perforation, including fatal cases, were reported when MOVANTIK was used in patients at risk of GI perforation (e.g., infiltrative gastrointestinal tract malignancy, recent gastrointestinal tract surgery, diverticular disease including diverticulitis, ischemic colitis, or concomitantly treated with bevacizumab). MOVANTIK is contraindicated in patients with known or suspected gastrointestinal obstruction or in patients at risk of recurrent obstruction [see Contraindications (4)] . Take into account the overall risk-benefit profile when using MOVANTIK in patients with these conditions or other conditions which might result in impaired integrity of the gastrointestinal tract wall (e.g., Crohn’s disease). Monitor for the development of severe, persistent or worsening abdominal pain; discontinue MOVANTIK in patients who develop this symptom.

6 ADVERSE REACTIONS

Serious and important adverse reactions described elsewhere in labeling include:

- Opioid withdrawal [see Warnings and Precautions (5.1)]
- Severe abdominal pain and/or diarrhea [see Warnings and Precautions (5.2)]
- Gastrointestinal perforation [see Warnings and Precautions (5.3)]

6.1 Clinical Trials Experience

Because clinical trials are conducted under widely varying conditions, adverse reaction rates observed in the clinical trials of a drug cannot be directly compared to rates in the clinical trials of another drug and may not reflect the rates observed in practice.

The data described below reflect exposure to MOVANTIK in 1497 patients in clinical trials, including 537 patients exposed for greater than six months, and 320 patients exposed for 12 months.

The safety data described in Table 1 are derived from two double-blind, placebo-controlled trials (Studies 1 and 2) in patients with OIC and non-cancer related pain [see Clinical Studies (14)] . Study 3 (n=302) was a safety extension study that allowed patients from Study 1 to continue the same blinded treatment for an additional 12 weeks. Safety data for patients in Study 3 are similar to those listed in Table 1. Study 4 (n=844) was a Phase 3, 52-week, multi-center, open-label, randomized, parallel group, safety and tolerability study of naloxegol versus usual care treatment for OIC (as determined by the investigator and excluding peripheral opioid antagonists) in patients with non-cancer related pain. The population enrolled in Study 4 was similar to that of the other studies. Eligible patients were randomized in a 2:1 ratio to receive either naloxegol 25 mg once daily or usual care treatment for OIC. The most commonly used laxatives in the usual care group were rectal stimulants (e.g., bisacodyl), oral stimulants (e.g., senna), and oral osmotics (e.g., macrogol, magnesium). Safety data for patients in Study 4 are similar to those listed in Table 1.

Table 1lists adverse reactions in pooled Studies 1 and 2 occurring in ≥3% of patients receiving MOVANTIK 12.5 mg or 25 mg and at an incidence greater than placebo.

Table 1. Adverse Reactions [Adverse reactions occurring in ≥3% of patients receiving MOVANTIK 12.5 mg or 25 mg and at an incidence greater than placebo.] in Patients with OIC and Non-Cancer Pain (Studies 1 and 2)
Adverse Reaction | MOVANTIK 25 mg; (n=446) | MOVANTIK 12.5 mg; (n=441) | Placebo; (n=444)
Abdominal Pain [Includes: abdominal pain, abdominal pain upper, abdominal pain lower, and gastrointestinal pain.] | 21% | 12% | 7%
Diarrhea | 9% | 6% | 5%
Nausea | 8% | 7% | 5%
Flatulence | 6% | 3% | 3%
Vomiting | 5% | 3% | 4%
Headache | 4% | 4% | 3%
Hyperhidrosis | 3% | <1% | <1%

Opioid Withdrawal

Possible opioid withdrawal, defined as at least three adverse reactions potentially related to opioid withdrawal that occurred on the same day and were not all related to the gastrointestinal system, occurred in less than 1% (1/444) of placebo subjects, 1% (5/441) receiving MOVANTIK 12.5 mg, and 3% (14/446) receiving MOVANTIK 25 mg in Studies 1 and 2 regardless of maintenance opioid treatment. Symptoms included but were not limited to hyperhidrosis, chills, diarrhea, abdominal pain, anxiety, irritability, and yawning. Patients receiving methadone as therapy for their pain condition were observed in Studies 1 and 2 to have a higher frequency of gastrointestinal adverse reactions than patients receiving other opioids [39% (7/18) vs. 26% (110/423) in the 12.5 mg group; 75% (24/32) vs. 34% (142/414) in the 25 mg group].

6.2 Postmarketing Experience

The following adverse reactions have been identified during post-approval use of MOVANTIK. Because reactions are reported voluntarily from a population of uncertain size, it is not always possible to reliably estimate the frequency or establish a causal relationship to drug exposure.

Hypersensitivity reactions: angioedema, rash, and urticaria.

Gastrointestinal disorders: Gastrointestinal perforation [see Warnings and Precautions (5.3)] .

7 DRUG INTERACTIONS

7.1 Effects of Other Drugs on MOVANTIK

Table 2displays the effects of other drugs on MOVANTIK.

Table 2. Effects of Other Drugs on MOVANTIK
Concomitant Agent | Mechanism of Action | Clinical Recommendation
CYP3A4 Inhibitors
•Strong CYP3A4 inhibitors (e.g., ketoconazole, itraconazole, clarithromycin) | •Increase plasma naloxegol concentrations and may increase the risk of adverse reactions [see Clinical Pharmacology (12.3)]. | •Use with strong CYP3A4 inhibitors is contraindicated [see Contraindications (4)] .
•Moderate CYP3A4 inhibitors (e.g., diltiazem, erythromycin, verapamil) | •Increase plasma naloxegol concentrations and may increase the risk of adverse reactions [see Clinical Pharmacology (12.3)]. | •Avoid use with moderate CYP3A4 inhibitors; if unavoidable, decrease the dosage of MOVANTIK to 12.5 mg once daily and monitor for adverse reactions [see Dosage and Administration (2.4)] .
•Weak CYP3A4 inhibitors (e.g., quinidine, cimetidine) | •Clinically significant increases in naloxegol concentrations are not expected. | •No dosage adjustments are necessary.
•Grapefruit or grapefruit juice [The effect of grapefruit juice varies widely among brands and is concentration-, dose-, and preparation-dependent. Studies have shown that it can be classified as a “strong CYP3A inhibitor” when a certain preparation was used (e.g., high dose, double strength) or as a “moderate CYP3A inhibitor” when another preparation was used (e.g., low dose, single strength).] | •Can increase plasma naloxegol concentrations. | •Avoid consumption of grapefruit or grapefruit juice during treatment with MOVANTIK [see Dosage and Administration (2.1)] .
CYP3A4 Inducers
•Strong CYP3A4 inducers (e.g., rifampin, carbamazepine, St. John’s Wort) | •Significantly decrease plasma naloxegol concentrations and may decrease the efficacy of MOVANTIK [see Clinical Pharmacology (12.3)] . | •Use with strong CYP3A4 inducers is not recommended .
Other Drug Interactions
•Other opioid antagonists | •Potential for additive effect of opioid receptor antagonism and increased risk of opioid withdrawal. | •Avoid use of MOVANTIK with another opioid antagonist.

8 USE IN SPECIFIC POPULATIONS

8.1 Pregnancy

Risk Summary

Limited available data with MOVANTIK use in pregnant women are insufficient to inform a drug associated risk of adverse developmental outcomes. MOVANTIK may precipitate opioid withdrawal in the pregnant women and the fetus (see Clinical Considerations) .

In animal development studies, no effects on embryo-fetal development were observed following administration of naloxegol in pregnant rats during the period of organogenesis at doses up to 1452 times the human AUC (area under the plasma concentration-time curve) at the maximum recommended human dose. No effects on embryo-fetal development were observed following administration of naloxegol in pregnant rabbits during the period of organogenesis at doses up to 409 times the human AUC at the maximum recommended human dose.

The estimated background risk of major birth defects and miscarriage for the indicated populations are unknown. All pregnancies have a background risk of birth defect, loss, or other adverse outcomes. In the U.S. general population, the estimated background risk of major birth defects and miscarriage in clinically-recognized pregnancies is 2% to 4% and 15% to 20%, respectively.

Clinical Considerations

Maternal and Fetal/Neonatal adverse reactions

The use of MOVANTIK may be associated with opioid withdrawal in the pregnant woman and the fetus.

Data

Animal Data

Oral administration of up to 750 mg/kg/day naloxegol in rats (1452 times the human AUC at the maximum recommended human dose) and 450 mg/kg/day naloxegol in rabbits (409 times the human AUC at the maximum recommended human dose) during the period of organogenesis produced no adverse effects on embryo-fetal development. Oral administration of up to 500 mg/kg/day in rats (195 times the maximum recommended human dose based on body surface area) during the period of organogenesis through lactation produced no adverse effects on parturition or the offspring.

8.2 Lactation

There are no data on the presence of naloxegol in human milk, the effects in nursing infants, or the effects on milk production. Naloxegol is present in rat milk (see Data). Because of the potential for adverse reactions, including opioid withdrawal in breastfed infants, advise women that breastfeeding is not recommended during treatment with MOVANTIK.

Data

Following oral administration of naloxegol in lactating rats, concentrations of naloxegol in milk were approximately 3- to 4-fold higher than concentrations of naloxegol in maternal plasma. Naloxegol was detected in plasma from pups.

8.4 Pediatric Use

The safety and effectiveness of MOVANTIK have not been established in pediatric patients.

8.5 Geriatric Use

Of the total number of subjects in clinical studies of MOVANTIK, 11% were 65 and over, while 2% were 75 and over. No overall differences in safety or effectiveness were observed between these subjects and younger subjects, and other reported clinical experience has not identified differences in responses between the elderly and younger patients, but greater sensitivity of some older individuals cannot be ruled out.

MOVANTIK exposure was higher in elderly healthy Japanese subjects compared to young subjects [see Clinical Pharmacology (12.3)] . No dosage adjustment is needed in elderly patients.

8.6 Renal Impairment

Some subjects with creatinine clearance (CLcr) values <60 mL/minute (i.e., moderate, severe, or end-stage renal disease) were shown to exhibit markedly higher systemic exposure of naloxegol compared to subjects with normal renal function. The reason for these high exposures is not understood. However, as the risk of adverse reactions increases with systemic exposure, a lower starting dosage of 12.5 mg once daily is recommended. No dosage adjustment is needed in patients with mild renal impairment [see Dosage and Administration (2.3)and Clinical Pharmacology (12.3)] .

8.7 Hepatic Impairment

The effect of severe hepatic impairment (Child-Pugh Class C) on the pharmacokinetics of naloxegol has not been evaluated. Avoid use of MOVANTIK in patients with severe hepatic impairment, as the dosage in these patients has not been determined. No dosage adjustment is required for patients with mild or moderate hepatic impairment [see Clinical Pharmacology (12.3)] .

10 OVERDOSAGE

In a clinical study of patients with OIC a daily dose of 50 mg (twice the recommended dosage), administered over 4 weeks, was associated with an increased incidence of GI adverse reactions, such as abdominal pain, diarrhea, and nausea. These adverse reactions frequently occurred within 1-2 days after dosing.

No antidote is known for naloxegol. Dialysis was noted to be ineffective as a means of elimination in a clinical study in patients with renal failure.

If a patient on opioid therapy receives an overdose of naloxegol, the patient should be monitored closely for potential evidence of opioid withdrawal symptoms such as chills, rhinorrhea, diaphoresis, or reversal of central analgesic effect. Base treatment on the degree of opioid withdrawal symptoms, including changes in blood pressure and heart rate, and on the need for analgesia.

11 DESCRIPTION

MOVANTIK (naloxegol), an opioid antagonist, contains naloxegol oxalate as the active ingredient. (Naloxegol is a PEGylated derivative of naloxone.)

The chemical name for naloxegol oxalate is: (5α,6α)-17-allyl-6-(2,5,8,11,14,17,20-heptaoxadocosan-22-yloxy)-4,5-epoxymorphinan-3,14-diol oxalate. The structural formula is:

The empirical formula for naloxegol oxalate is C34H53NO11.C2H2O4and the molecular weight is 742.

Naloxegol oxalate is a white to off-white powder, with high aqueous solubility across the physiologic pH range.

MOVANTIK (naloxegol) tablets for oral use contain 14.2 mg and 28.5 mg of naloxegol oxalate, respectively, equivalent to 12.5 mg and 25 mg of naloxegol.

Excipients in tablet core are: mannitol, cellulose microcrystalline, croscarmellose sodium, magnesium stearate, and propyl gallate.

Excipients in tablet coat are: hypromellose, titanium dioxide, polyethylene glycol, iron oxide red, and iron oxide black.

12 CLINICAL PHARMACOLOGY

12.1 Mechanism of Action

Naloxegol is an antagonist of opioid binding at the mu-opioid receptor. When administered at the recommended dose levels, naloxegol functions as a peripherally-acting mu-opioid receptor antagonist in tissues, such as the gastrointestinal tract, thereby decreasing the constipating effects of opioids.

Naloxegol is a PEGylated derivative of naloxone and is a substrate for the P-glycoprotein transporter (P-gp). Also, the presence of the PEG moiety in naloxegol reduces its passive permeability as compared with naloxone. Due to the reduced permeability and increased efflux of naloxegol across the blood-brain barrier, related to P-gp substrate properties, the CNS penetration of naloxegol is expected to be negligible at the recommended dose levels limiting the potential for interference with centrally mediated opioid analgesia.

12.2 Pharmacodynamics

Use of opioids induces slowing of gastrointestinal motility and transit. Antagonism of gastrointestinal mu-opioid receptors by naloxegol inhibits opioid-induced delay of gastrointestinal transit time.

Effect on Cardiac Repolarization

In a randomized, double-blind, 4-way cross-over thorough QTc prolongation study with moxifloxacin as a positive control, a single 25 mg therapeutic dose or a 150 mg dose (6 times the maximum recommended dosage) of naloxegol did not have an effect on the QTc interval compared to placebo. Changes in heart rate, RR, PR, and QRS ECG intervals were similar between placebo and naloxegol 25 or 150 mg.

Exposure Response Analysis

The exposure-response analysis for adverse events showed that the probability of experiencing abdominal pain increased with increasing naloxegol exposure over the dose range of 12.5 mg to 25 mg once a day. The exposure-response analysis for efficacy conducted using the definition of response in the clinical trials [see Clinical Studies (14)] indicated that response was similar over this dose range.

12.3 Pharmacokinetics

Absorption

Following oral administration, MOVANTIK is absorbed with peak concentrations (Cmax) achieved at less than 2 hours. In a majority of subjects, a secondary plasma concentration peak of naloxegol was observed approximately 0.4 to 3 hours after the first peak. Across the range of doses evaluated, peak plasma concentration and area under the plasma concentration-time curve (AUC) increased in a dose-proportional or almost dose-proportional manner. Accumulation was minimal following multiple daily doses of naloxegol.

MOVANTIK as a crushed tablet mixed in water, given orally or administered through a nasogastric tube into the stomach, provides systemic naloxegol concentrations that are comparable to the whole tablet, with a median tmaxof 0.75 and 1.5 hours (range 0.25 to 5 hours) for the crushed tablet given orally and the crushed tablet given via nasogastric (NG) tube, respectively [see Dosage and Administration (2.2)] .

Food Effects

A high-fat meal increased the extent and rate of naloxegol absorption. The Cmaxand AUC were increased by approximately 30% and 45%, respectively. In clinical trials, naloxegol was dosed on an empty stomach approximately 1 hour prior to the first meal in the morning.

Distribution

The mean apparent volume of distribution during the terminal phase (Vz/F) in healthy volunteers ranged from 968 L to 2140 L across dosing groups and studies. Plasma protein binding of naloxegol in humans was low (~4.2%).

Metabolism

Naloxegol is metabolized primarily by the CYP3A enzyme system. In a mass balance study in humans, a total of 6 metabolites were identified in plasma, urine, and feces. These metabolites were formed via N-dealkylation, O-demethylation, oxidation, and partial loss of the PEG chain. Human metabolism data suggests absence of major metabolites. The activity of the metabolites at the opioid receptor has not been determined.

Excretion

Following oral administration of radio-labeled naloxegol, 68% and 16% of total administered dose were recovered in the feces and urine, respectively. Parent naloxegol excreted in the urine accounted for less than 6% of the total administered dose. Approximately 16% of radioactivity in feces was noted to be unchanged naloxegol, while the remaining was attributed to metabolites. Thus, renal excretion is a minor clearance pathway for naloxegol. In a clinical pharmacology study, the half-life of naloxegol at therapeutic doses ranged from 6 to 11 hours.

Specific Populations

Renal Impairment:

The effect of renal impairment on the pharmacokinetics of a 25 mg single oral dose of MOVANTIK was studied in subjects with renal impairment (RI) classified as moderate (n=8), severe (n=4), or end-stage renal disease (ESRD) not yet on dialysis (n=4), and compared with healthy subjects (n=6). Most renal impairment (RI) subjects (6 out of 8 with moderate RI, 3 out of 4 with severe RI, and 3 out of 4 with ESRD) had plasma naloxegol pharmacokinetics comparable to those in healthy subjects. The remaining individuals with renal impairment demonstrated higher naloxegol exposures (up to 10-fold) compared to the control group. The reason for these high exposures is unknown.

This study also included 8 ESRD patients on hemodialysis. Plasma concentrations of naloxegol in these subjects were similar to healthy volunteers with normal renal function, when MOVANTIK was administered either pre- or post-hemodialysis [see Dosage and Administration (2.3), Use in Specific Populations (8.6), and Overdosage (10)] .

Hepatic Impairment:

Slight decreases in AUC of naloxegol were observed in subjects with mild and moderate hepatic impairment (Child-Pugh Classes A and B; n=8 per group) compared to subjects with normal hepatic function (n=8), following administration of a single 25 mg oral dose of MOVANTIK. The effect of severe hepatic impairment (Child-Pugh Class C) on the pharmacokinetics of naloxegol was not evaluated [see Use in Specific Populations (8.7)] .

Age:

The mean Cmax,ssand AUCτ,ssvalues seen in elderly healthy Japanese subjects (n=6) were approximately 45% and 54% greater than those obtained in young healthy subjects (n=6) following multiple daily doses of naloxegol (25 mg).

Gender:

There is no gender effect on the pharmacokinetics of naloxegol.

Race:

When compared to Caucasian subjects, naloxegol AUC was approximately 20% lower in Blacks and Cmaxwas approximately 10% lower and 30% higher in Blacks and Asians, respectively.

Drug Interaction Studies

Effect of MOVANTIK on Other Drugs

In in vitrostudies at clinically relevant concentrations, naloxegol did not show a significant inhibitory effect on the activity of CYP1A2, CYP2C8, CYP2C9, CYP2D6, CYP3A4 or CYP2C19, nor a significant induction effect on the activity of CYP1A2, CYP2B6, or CYP3A4. Therefore, MOVANTIK is not expected to alter the metabolic clearance of co-administered drugs that are metabolized by these enzymes. Naloxegol is not a significant inhibitor of P-gp, BCRP, OAT1, OAT3, OCT2, OATP1B1, and OATP1B3.

In healthy subjects receiving morphine 5 mg/70 kg intravenously, single doses of MOVANTIK ranging from 8 mg to 1000 mg were given concomitantly with 5 to 6 subjects per dose cohort. With increasing MOVANTIK dose, there was no increasing or decreasing trend in morphine exposure compared to morphine administered alone. An analysis of the pooled data indicated that MOVANTIK had no meaningful impact on the systemic exposure of morphine and its major circulating metabolites.

Effect of Other Drugs on MOVANTIK

Naloxegol is metabolized mainly by CYP3A enzymes and is a substrate of P-gp transporter. The effects of co-administered drugs on the pharmacokinetics of naloxegol are summarized in Figure 1 [see Drug Interactions (7.1)] .

The effects of once daily oral dosing of 400 mg ketoconazole, once daily oral dosing of 600 mg rifampicin and once daily oral dosing of 240 mg diltiazem (as an extended release formulation) on the pharmacokinetics of 25 mg MOVANTIK were studied following multiple dosing and at steady state exposure of the perpetrator drugs. The effects of 600 mg oral dosing of quinidine and intravenous morphine (5 mg/70 kg) on the pharmacokinetics of 25 mg MOVANTIK were studied following single dosing of the perpetrator drugs.

Figure 1: Effect of Co-administered Drugs on the Pharmacokinetics of Naloxegol

*Quinidine due to its effect on P-gp transporter increased naloxegol Cmaxby 2.5-fold; the AUC increased by 1.4-fold; no dosage adjustment is necessary.

No drug interaction studies have been conducted for MOVANTIK with drugs that alter gastric pH (e.g., antacids, proton-pump inhibitors).

Simulations using physiologically based pharmacokinetic modeling, suggested that naloxegol exposures after co-administration of a single oral 25 mg dose of MOVANTIK with a moderate CYP3A inducer efavirenz (400 mg once a day) are similar to those after 12.5 mg MOVANTIK alone.

13 NONCLINICAL TOXICOLOGY

13.1 Carcinogenesis, Mutagenesis, Impairment of Fertility

Carcinogenesis

In a 104-week carcinogenicity study in CD-1 mice, naloxegol was not tumorigenic at oral doses up to 100 mg/kg/day in males and 160 mg/kg/day in females (43 and 27 times the human AUC at the maximum recommended human dose for male and female mice, respectively). In a carcinogenicity study in Sprague-Dawley rats, naloxegol was administered orally at doses of 40, 120, and 400 mg/kg/day for at least 93 weeks. Naloxegol did not cause an increase in tumors in female rats. In male rats, an increase in interstitial (Leydig) cell adenomas in testes was observed at 400 mg/kg/day (818 times the human AUC at the maximum recommended human dose). The no observed effect level for increased tumor incidence was 120 mg/kg/day in male and 400 mg/kg/day in female rats (246 and 1030 times the human AUC at the maximum recommended human dose for male and female rats, respectively). The Leydig cell neoplasms in rats are considered to be unlikely relevant to humans.

Mutagenesis

Naloxegol was not genotoxic in the in vitrobacterial reverse mutation (Ames) assay, mouse lymphoma TK+/-mutation assay, or the in vivomouse micronucleus assay.

Impairment of Fertility

Naloxegol was found to have no effect on fertility or reproductive performance in male and female rats at oral doses up to 1000 mg/kg/day (greater than 1000 times the human AUC at the maximum recommended human dose).

14 CLINICAL STUDIES

The safety and efficacy of MOVANTIK were evaluated in two replicate, randomized, double-blind placebo-controlled trials (Study 1 and Study 2) in patients with opioid-induced constipation (OIC) and non-cancer related pain.

Patients receiving an opioid morphine equivalent daily dose of between 30 mg and 1,000 mg for at least four weeks before enrollment and self-reported OIC were eligible to participate. OIC was confirmed through a two-week run-in period and was defined as <3 spontaneous bowel movements (SBMs) per week on average with at least 25% of the SBMs associated with one or more of the following conditions: (1) straining, (2) hard or lumpy stools; and (3) having a sensation of incomplete evacuation. An SBM was defined as a bowel movement (BM) without rescue laxative taken within the past 24 hours. Patients with 0 BMs over the two-week run-in period or patients with an uneven distribution of SBMs across the two-week run-in period (0 SBMs in one week with ≥4 SBMs in the other week) were excluded. Throughout the studies (including the two-week run-in period), patients were prohibited from using laxatives other than bisacodyl rescue laxative (if they had not had a BM for 72 hours) and one-time use of an enema (if after 3 doses of bisacodyl, they still did not have a BM).

Patients suspected of having clinically important disruptions to the blood-brain barrier were not enrolled in these studies.

A total of 652 patients in Study 1 and 700 patients in Study 2 were randomized in a 1:1:1 ratio to receive 12.5 mg or 25 mg of MOVANTIK or placebo once daily for 12 weeks.

The mean age of the subjects in these two studies was 52 years, 10% and 13% were 65 years of age or older, 61% and 63% were women, and 78% and 80% were White in Studies 1 and 2, respectively.

Back pain was the most common reason for pain (56% and 57%); arthritis (10% and 10%) and joint pain (3% and 5%) were other prominent reasons in Studies 1 and 2, respectively. Prior to enrollment, patients had been using their current opioid for an average of 3.6 and 3.7 years. The patients who participated in Studies 1 and 2 were taking a wide range of opioids. The mean baseline opioid morphine equivalent daily dosage was 140 mg and 136 mg per day.

Use of one or more laxatives on at least one occasion within the two weeks prior to enrollment was reported by 71% of patients in both Studies 1 and 2.

The primary endpoint was response defined as: ≥3 SBMs per week and a change from baseline of ≥1 SBM per week for at least 9 out of the 12 study weeks and 3 out of the last 4 weeks.

There was a statistically significant difference for the 25 mg MOVANTIK treatment group versus placebo for the primary endpoint in Study 1 and Study 2 (see Table 3). Statistical significance for the 12.5 mg treatment group versus placebo was observed in Study 1 but not in Study 2 (see Table 3).

Table 3. Primary Endpoint: Response [Response defined as: ≥3 SBMs per week and change from baseline of ≥1 SBM per week for at least 9 out of the 12 study weeks and 3 out of the last 4 weeks.] (Studies 1 and 2)
 | Study 1
 | Placebo (N = 214) | 12.5 mg (N = 213) | 25 mg (N = 214)
Patients responding, n (%) | 63 (29%) | 87 (41%) | 95 (44%)
Treatment Difference (MOVANTIK-Placebo) | -- | 11.4% | 15.0%
95% Confidence Interval | -- | (2.4%, 20.4%) | (5.9%, 24.0%)
p-value | -- | 0.015 [Statistically significant: p-values based on the Cochran-Mantel-Haenszel test.] | 0.001
 | Study 2
 | Placebo (N = 232) | 12.5 mg (N = 232) | 25 mg (N = 232)
Patients responding, n (%) | 68 (29%) | 81 (35%) | 92 (40%)
Treatment Difference (MOVANTIK-Placebo) | -- | 5.6% | 10.3%
95% Confidence Interval | -- | (-2.9%, 14.1%) | (1.7%, 18.9%)
p-value | -- | 0.202 | 0.021

One secondary endpoint in Study 1 and Study 2 was response in laxative users with OIC symptoms. This subgroup comprised 55% and 53% of total patients in these two studies, respectively. These patients (identified using an investigator-administered questionnaire), prior to enrollment, had reported using laxative(s) at least 4 out of the past 14 days with at least one of the following OIC symptoms of moderate, severe, or very severe intensity: incomplete bowel movements, hard stool, straining, or sensation of needing to pass a bowel movement but unable to do so. In this subgroup, in Studies 1 and 2, 42% and 50% reported using laxatives on a daily basis. The most frequently reported laxatives used on a daily basis were stool softeners (18% and 24%), stimulants (16% and 18%), and polyethylene glycol (6% and 5%). Use of two laxative classes was reported in 31% and 27% anytime during the 14 days prior to enrollment. The most commonly reported combination was stimulants and stool softeners (10% and 8%). In Study 1, a statistically significantly higher percentage of patients in this subgroup responded with MOVANTIK 12.5 mg compared to placebo (43% vs. 29%; p=0.03) and with MOVANTIK 25 mg compared to placebo (49% vs. 29%; p=0.002). In Study 2, a statistically significantly higher percentage of patients in this subgroup responded with MOVANTIK 25 mg compared to placebo (47% vs. 31%; p=0.01). This secondary endpoint was not tested for MOVANTIK 12.5 mg versus placebo in Study 2 because the primary endpoint was not statistically significant.

Another secondary endpoint was time to first post-dose SBM. The time to first post-dose SBM was significantly shorter with MOVANTIK 25 mg compared to placebo in both Study 1 (p <0.001) and Study 2 (p <0.001), and for MOVANTIK 12.5 mg as compared to placebo in Study 1 (p <0.001). For Study 1, the median times to first post-dose SBM were 6, 20, and 36 hours with MOVANTIK 25 mg, MOVANTIK 12.5 mg, and placebo, respectively. For Study 2, the median times to first post-dose SBM were 12 and 37 hours with MOVANTIK 25 mg and placebo, respectively. These analyses do not include the results for MOVANTIK 12.5 mg versus placebo in Study 2 because the primary endpoint was not statistically significant. In the two studies, 61-70% and 58% of patients receiving MOVANTIK 25 mg and MOVANTIK 12.5 mg, respectively, had an SBM within 24 hours of the first dose.

A third secondary endpoint was an evaluation of change from baseline between the treatment groups for mean number of days per week with at least 1 SBM but no more than 3 SBMs. There was a significant difference in number of days per week with 1 to 3 SBMs per day on average over 12 weeks between MOVANTIK 25 mg (Study 1 and Study 2) and MOVANTIK 12.5 mg (Study 1) and placebo.

16 HOW SUPPLIED/STORAGE AND HANDLING

MOVANTIK (naloxegol) tablets are supplied as:

- NDC 82625-8801-1: 12.5 mg, bottle of 30 tablets
- NDC 82625-8801-2: 12.5 mg, bottle of 90 tablets
- NDC 82625-8801-3: 12.5 mg, unit dose blister carton of 100 tablets (for HUD only)
- NDC 82625-8802-1: 25 mg, bottle of 30 tablets
- NDC 82625-8802-2: 25 mg, bottle of 90 tablets
- NDC 82625-8802-3: 25 mg, unit dose blister carton of 100 tablets (for HUD only)

Storage

Store MOVANTIK at 20-25°C (68-77°F). Excursions permitted to 15-30°C (59-86°F) [see USP Controlled Room Temperature].

17 PATIENT COUNSELING INFORMATION

Advise the patient to read the FDA-approved patient labeling (Medication Guide).

Administration

Advise patients to:

- Discontinue all maintenance laxative therapy prior to initiation of MOVANTIK. Laxative(s) can be used as needed if there is a suboptimal response to MOVANTIK after three days.
- Take MOVANTIK on an empty stomach at least 1 hour prior to the first meal of the day or 2 hours after the meal.
- Discontinue MOVANTIK if treatment with the opioid pain medication is also discontinued.
- Avoid consumption of grapefruit or grapefruit juice during treatment with MOVANTIK.
- Inform their healthcare provider if their opioid pain medication is discontinued.
- Inform their healthcare provider if they are unable to tolerate MOVANTIK, so a dosage adjustment can be considered.
- If patients are unable to swallow the MOVANTIK tablet whole, the tablet can be crushed to a powder, mixed with water and administered orally or via a nasogastric (NG) tube, as described in the Medication Guide.

Drug Interactions

Advise patients to tell their healthcare provider when they start or stop taking any concomitant medications. Strong CYP3A4 inhibitors (e.g., clarithromycin, ketoconazole) are contraindicated with MOVANTIK, and other CYP3A4 enzyme modulating drugs can alter MOVANTIK exposure [see Contraindications (4)and Drug Interactions (7.1)].

Opioid Withdrawal

Advise patients that clusters of symptoms consistent with opioid withdrawal may occur while taking MOVANTIK, including sweating, chills, diarrhea, abdominal pain, anxiety, irritability, and yawning. Inform patients taking methadone as therapy for their pain condition that they may be more likely to have gastrointestinal adverse reactions such as abdominal pain and diarrhea that may be related to opioid withdrawal, than patients receiving other opioids [see Warnings and Precautions (5.1)].

Severe Abdominal Pain and/or Diarrhea

Advise patients that symptoms may occur after starting treatment. The patient should discontinue MOVANTIK and contact their healthcare provider if they develop severe abdominal pain and/or diarrhea [see Warnings and Precautions (5.2)] .

Gastrointestinal Perforation

Advise patients to discontinue MOVANTIK and promptly seek medical attention if they develop unusually severe, persistent or worsening abdominal pain [see Warnings and Precautions (5.3)] .

Pregnancy

Advise females of reproductive potential, who become pregnant or are planning to become pregnant that the use of MOVANTIK during pregnancy may precipitate opioid withdrawal in the pregnant women and the fetus [see Use in Specific Populations (8.1)] .

Lactation

Advise females that breastfeeding is not recommended during treatment with MOVANTIK [see Use in Specific Populations (8.2)].

MOVANTIK is a registered trademark of the AstraZeneca Group of companies and used under license by Valinor Pharma, LLC.

Distributed by: Valinor Pharma, LLC, Chicago, IL 60606

© 2023 Valinor Pharma, LLC

MEDICATION GUIDE

MOVANTIK®(mo-van-tic)

(naloxegol)

tablets, for oral use

Read this Medication Guide before you start taking MOVANTIK and each time you get a refill. There may be new information. This information does not take the place of talking with your healthcare provider about your medical condition or your treatment.

What is the most important information I should know about MOVANTIK?

MOVANTIK may cause serious side effects, including:

- Opioid withdrawal.You may have symptoms of opioid withdrawal during treatment with MOVANTIK including sweating, chills, diarrhea, stomach pain, anxiety, irritability, and yawning. If you take methadone to treat your pain, you may be more likely to have stomach pain and diarrhea than people who do not take methadone. Tell your health care provider if you have any of these symptoms.
- Severe stomach pain or diarrhea, or both severe stomach pain and diarrhea.Severe stomach pain and diarrhea can happen when you take MOVANTIK. These problems can happen within a few days after you start taking MOVANTIK and can lead to hospitalization. Stop taking MOVANTIK and call your healthcare provider right away if you have severe stomach pain or diarrhea, or both severe stomach pain and diarrhea.
- Tear in your stomach or intestinal wall (perforation).Stomach pain that is severe can be a sign of a serious medical condition. If you have stomach pain that gets worse or does not go away, stop taking MOVANTIK and get emergency medical help right away.

What is MOVANTIK?

MOVANTIK is a prescription medicine used to treat constipation that is caused by prescription pain medicines called opioids, in adults with long-lasting (chronic) pain that is not caused by active cancer.

It is not known if MOVANTIK is safe and effective in children.

Who should not take MOVANTIK?

Do not take MOVANTIK if you:

- have a bowel blockage (intestinal obstruction) or have a history of bowel blockage.
- are allergic to MOVANTIK or any of the ingredients in MOVANTIK. See the end of this Medication Guide for a complete list of ingredients in MOVANTIK.

MOVANTIK can interact with certain other medicines and cause side effects, including opioid withdrawal symptoms such as sweating, chills, diarrhea, stomach pain, anxiety, irritability, and yawning. Tell your healthcare provider or pharmacist before you start or stop any medicines during treatment with MOVANTIK.

What should I tell my healthcare provider before taking MOVANTIK?

Before you take MOVANTIK, tell your healthcare provider about all of your medical conditions, including if you:

- have any stomach or bowel (intestines) problems, including inflammation in parts of the large intestine (diverticulitis), inflammation and injury of the intestines caused by reduced blood flow (ischemic colitis), or cancer of the stomach or bowel.
- have had recent surgery on the stomach or intestines.
- have kidney problems.
- have liver problems.
- are pregnant or plan to become pregnant. Taking MOVANTIK during pregnancy may cause opioid withdrawal symptoms in you or your unborn baby. Tell your healthcare provider right away if you become pregnant during treatment with MOVANTIK.
- are breastfeeding or plan to breastfeed. It is not known if MOVANTIK passes into your breast milk.
- taking MOVANTIK while you are breastfeeding may cause opioid withdrawal in your baby. You and your healthcare provider should decide if you will take MOVANTIK or breastfeed. You should not breastfeed if you take MOVANTIK.

Tell your healthcare provider about all of the medicines you take, including prescription and over-the-counter medicines, vitamins, and herbal supplements. Other medicines may affect the way MOVANTIK works.

Especially tell your healthcare provider if you takea medicine called bevacizumab.

How should I take MOVANTIK?

- Take MOVANTIK exactly as your healthcare provider tells you.
- Take your prescribed dose of MOVANTIK 1 time each day, on an empty stomach, at least 1 hour before your first meal of the day or 2 hours after the meal.
- If you cannot swallow MOVANTIK tablets whole, MOVANTIK can be mixed with water and taken by mouth or given through a nasogastric (NG) tube. To take MOVANTIK by mouth:

∘crush the tablet to a powder

∘place your dose of MOVANTIK in a glass that contains 4 ounces (120 mL) of water and stir

∘swallow MOVANTIK and water mixture right away

∘add 4 more ounces (120 mL) of water to the glass and drink right away, to make sure that you take your full dose of MOVANTIK

- If you cannot swallow MOVANTIK tablets and have a nasogastric (NG) tube, MOVANTIK may be given as follows:

∘draw up 1 ounce (30 mL) of water into a 60 mL syringe and flush the NG tube∘crush the tablet to a powder

∘place your dose of MOVANTIK in a container and mix with approximately 2 ounces (60 mL) of water∘draw up the MOVANTIK and water into the 60 mL syringe and give the mixture through the NG tube

∘add approximately 2 ounces (60 mL) of water to the same container you used to prepare your dose of MOVANTIK

∘draw up the water using the same 60 mL syringe and use all the water to flush the NG tube and any remaining medicine from the NG tube into the stomach

- Stop taking other laxatives before you start treatment with MOVANTIK. Your healthcare provider may prescribe other laxatives if MOVANTIK does not work after 3 days of treatment.
- MOVANTIK has been shown to be effective in people who have taken opioid pain medicines for at least 4 weeks.
- Tell your healthcare provider if you stop taking your opioid pain medicine. If you stop taking your opioid pain medicine, you should also stop taking MOVANTIK.
- If you take too much MOVANTIK, call your healthcare provider or go to the nearest emergency room right away.

What should I avoid while taking MOVANTIK?

- Avoid eating grapefruit or drinking grapefruit juice during treatment with MOVANTIK.

What are the possible side effects of MOVANTIK?

See “What is the most important information I should know about MOVANTIK?”

The most common side effects of MOVANTIK include:stomach (abdomen) pain, diarrhea, nausea, gas, vomiting, and headache.

Tell your healthcare provider if you have any side effect that bothers you or that does not go away. These are not all the possible side effects of MOVANTIK.

Call your doctor for medical advice about side effects. You may report side effects to FDA at 1-800-FDA-1088.

How should I store MOVANTIK?

- Store MOVANTIK at room temperature between 68°F to 77°F (20°C to 25°C).
- Safely throw away medicine that is out of date or that you no longer need.

Keep MOVANTIK and all medicines out of the reach of children.

General information about the safe and effective use of MOVANTIK.

Medicines are sometimes prescribed for purposes other than those listed in a Medication Guide. Do not use MOVANTIK for a condition for which it was not prescribed. Do not give MOVANTIK to other people, even if they have the same symptoms that you have. It may harm them. You can ask your pharmacist or healthcare provider for information about MOVANTIK that is written for health professionals.

What are the ingredients in MOVANTIK?

Active ingredient:naloxegol oxalate

Inactive ingredients:The tablet core contains mannitol, cellulose microcrystalline, croscarmellose sodium, magnesium stearate, and propyl gallate. The tablet coat contains hypromellose, titanium dioxide, polyethylene glycol, iron oxide red, and iron oxide black.

Distributed by: Valinor Pharma, LLC, Chicago, IL 60606

MOVANTIK is a registered trademark of the AstraZeneca Group of companies and used under license by Valinor Pharma, LLC. © 2023 Valinor Pharma, LLC. All rights reserved.

For more information, go to www.MOVANTIK.comor call 1-877-592-2337.

This Medication Guide has been approved by the U.S. Food and Drug Administration. Revised: 03/2023

PACKAGE/LABEL PRINCIPAL DISPLAY PANEL – 12.5 mg

NDC 82625-8801-1 30 Tablets

movantik®

(naloxegol) Tablets

12.5 mg*

*Each tablet contains 14.2 mg
naloxegol oxalate

Dispense the accompanying
Medication Guide to each patient.

Rx only

Valinor

PACKAGE/LABEL PRINCIPAL DISPLAY PANEL – 25 mg

NDC 82625-8802-1 30 Tablets

movantik®

(naloxegol) Tablets

25 mg*

*Each tablet contains 28.5 mg
naloxegol oxalate

Dispense the accompanying
Medication Guide to each patient.

Rx only

Valinor